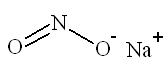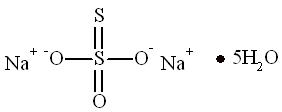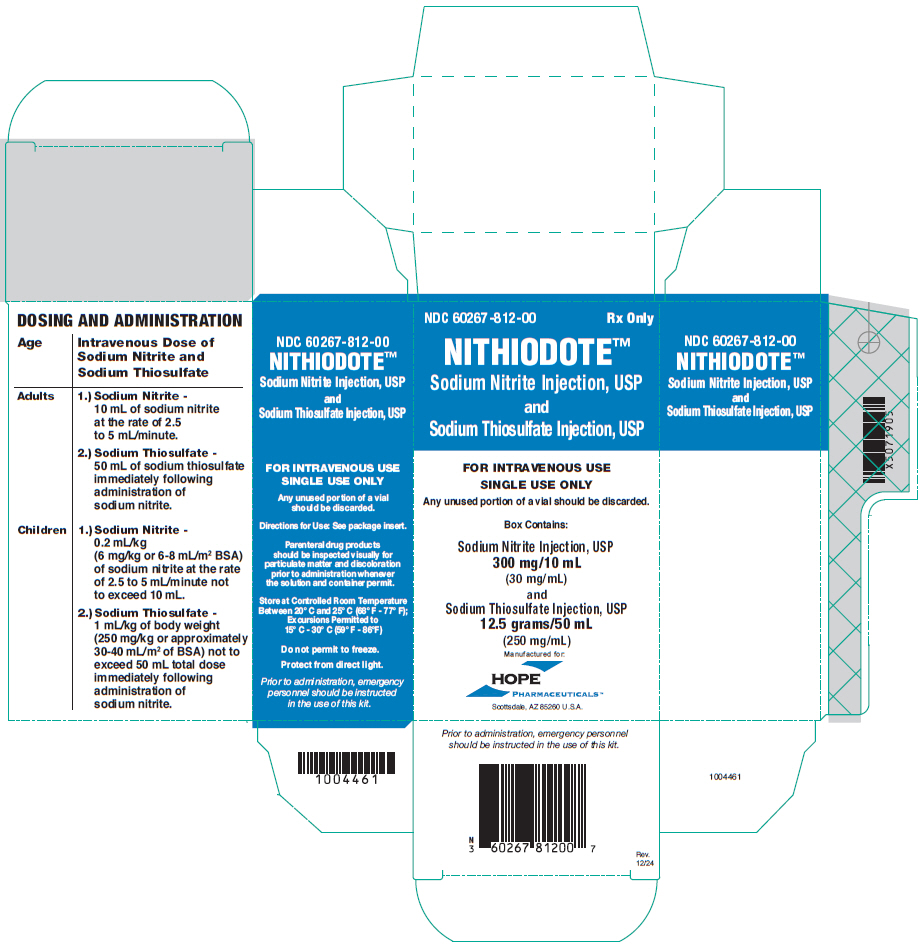 DRUG LABEL: NITHIODOTE
NDC: 60267-812 | Form: KIT | Route: INTRAVENOUS
Manufacturer: Hope Pharmaceuticals
Category: prescription | Type: HUMAN PRESCRIPTION DRUG LABEL
Date: 20251006

ACTIVE INGREDIENTS: Sodium Nitrite 30 mg/1 mL; Sodium Thiosulfate 250 mg/1 mL
INACTIVE INGREDIENTS: Water; Nitrogen; Potassium Chloride 4.4 mg/1 mL; Boric Acid 2.8 mg/1 mL; Water; Sodium Hydroxide; Nitrogen

HIGHLIGHTS OF PRESCRIBING INFORMATION

These highlights do not include all the information needed to use the NITHIODOTE safely and effectively. See full prescribing information for NITHIODOTE.
NITHIODOTE (sodium nitrite injection and sodium thiosulfate injection for intravenous infusion).
Initial U.S. Approval: 1992

WARNING: LIFE THREATENING HYPOTENSION AND METHEMOGLOBIN FORMATION

See full prescribing information for complete boxed warning.

Sodium nitrite can cause serious adverse reactions and death from:

- Hypotension (5.1)
- Methemoglobin formation (5.2)

Patients should be closely monitored to ensure adequate perfusion and oxygenation during treatment with sodium nitrite.

1 INDICATIONS AND USAGE

NITHIODOTE, an antidote, is indicated for the treatment of acute cyanide poisoning that is judged to be serious or life-threatening. (1)

- Use with caution if the diagnosis of cyanide poisoning is uncertain. (1)

2 DOSAGE AND ADMINISTRATION

- If clinical suspicion of cyanide poisoning is high, administer NITHIODOTE without delay and in conjunction with appropriate airway, ventilatory, and circulatory support. (2.1)
- The expert advice of a regional poison control center may be obtained by calling 1-800-222-1222. (2.1)

Dosing:

Age | Intravenous Dose of Sodium Nitrite and Sodium Thiosulfate
Adults | 1) Sodium Nitrite -10 mL of sodium nitrite at the rate of 2.5 to 5 mL/minute 2) Sodium Thiosulfate - 50 mL of sodium thiosulfate immediately following administration of sodium nitrite.
Children | 1) Sodium Nitrite - 0.2 mL/kg (6 mg/kg or 6-8 mL/m^2 BSA) of sodium nitrite at the rate of 2.5 to 5 mL/minute not to exceed 10 mL 2) Sodium Thiosulfate - 1 mL/kg of body weight (250 mg/kg or approximately 30-40 mL/m^2 of BSA) not to exceed 50 mL total dose immediately following administration of sodium nitrite.

- Redosing: If signs of cyanide poisoning reappear, repeat treatment using one-half the original dose of both sodium nitrite and sodium thiosulfate. (2.2)
- Monitoring: Blood pressure must be monitored during treatment. (2.2)
- NITHIODOTE is chemically incompatible with hydroxocobalamin and should not be administered via the same intravenous line. (2.4)

3 DOSAGE FORMS AND STRENGTHS

NITHIODOTE consists of:

- one vial of sodium nitrite injection, USP 300 mg/10 mL (30 mg/mL) and
- one vial of sodium thiosulfate injection, USP 12.5 grams/50 mL (250 mg/mL). (3)

4 CONTRAINDICATIONS

- None. (4)

5 WARNINGS AND PRECAUTIONS

- Methemoglobinemia: Sodium nitrite reacts with hemoglobin to form methemoglobin and should be used with caution in patients known to have anemia. Monitor oxyhemoglobin and methemoglobin levels by pulse co-oximetry or other measurements. Optimally, the sodium nitrite dose should be reduced in proportion to the oxygen carrying capacity. (5.2)
- Smoke inhalation: Carbon monoxide contained in smoke can result in the formation of carboxyhemoglobin that can reduce the oxygen carrying capacity of the blood. Sodium nitrite should be used with caution in patients with smoke inhalation injury because of the potential for worsening hypoxia due to methemoglobin formation.
  Carboxyhemoglobin and oxyhemoglobin levels should be monitored by pulse oximetry or other measurements in patients that present with evidence of smoke inhalation. Optimally, the sodium nitrite dose should be reduced in proportion to the oxygen carrying capacity. (5.4)

6 ADVERSE REACTIONS

Most common adverse reactions are:

- Sodium nitrite: syncope, hypotension, tachycardia, palpitations, dysrhythmia, methemoglobinemia, headache, dizziness, blurred vision, seizures, confusion, coma (6)
- Sodium thiosulfate: hypotension, headache, disorientation (6)

To report SUSPECTED ADVERSE REACTIONS, contact Hope Pharmaceuticals at 1-800-755-9595 or FDA at 1-800-FDA-1088 or www.fda.gov/medwatch.

8 USE IN SPECIFIC POPULATIONS

- Lactation: Breastfeeding not recommended. (8.2)
- Renal impairment: Sodium nitrite and sodium thiosulfate are substantially excreted by the kidney. The risk of toxic reactions to these drugs may be greater in patients with impaired renal function. (8.6).

FULL PRESCRIBING INFORMATION

WARNING: LIFE THREATENING HYPOTENSION AND METHEMOGLOBIN FORMATION

Sodium nitrite can cause serious adverse reactions and death in humans, even at doses less than twice the recommended therapeutic dose. Sodium nitrite causes hypotension and methemoglobin formation, which diminishes oxygen carrying capacity. Hypotension and methemoglobin formation can occur concurrently or separately. Because of these risks, sodium nitrite should be used to treat acute life-threatening cyanide poisoning and be used with caution in patients where the diagnosis of cyanide poisoning is uncertain.

Patients should be closely monitored to ensure adequate perfusion and oxygenation during treatment with sodium nitrite.

Alternative therapeutic approaches should be considered in patients known to have diminished oxygen or cardiovascular reserve (e.g. smoke inhalation victims, pre-existing anemia, cardiac or respiratory compromise), and those at higher risk of developing methemoglobinemia (e.g., congenital methemoglobin reductase deficiency) as they are at greater risk for potentially life-threatening adverse events related to the use of sodium nitrite. [See Warnings and Precautions (5.1 and 5.2)]

1 INDICATIONS AND USAGE

NITHIODOTE is indicated for the treatment of acute cyanide poisoning that is judged to be serious or life-threatening. When the diagnosis of cyanide poisoning is uncertain, carefully weigh the potentially life-threatening risks associated with NITHIODOTE against the potential benefits, especially if the patient is not in extremis.

2 DOSAGE AND ADMINISTRATION

2.1 Important Dosage and Administration Instructions

- If clinical suspicion of cyanide poisoning is high, administer NITHIODOTE without delay.
- Comprehensive treatment of acute cyanide intoxication requires support of vital functions. Administration of sodium nitrite and sodium thiosulfate should be considered adjunctive to appropriate supportive therapies. Airway, ventilatory and circulatory support, and oxygen administration should not be delayed in order to administer sodium nitrite and sodium thiosulfate [see Warnings and Precautions (5.1)].
- The expert advice of a regional poison control center may be obtained by calling 1-800-222-1222.

Identifying Patients with Cyanide Poisoning

Cyanide poisoning may result from inhalation, ingestion, or dermal exposure to various cyanide-containing compounds, including smoke from closed-space fires. Sources of cyanide poisoning include hydrogen cyanide and its salts, cyanogenic plants, aliphatic nitriles, and prolonged exposure to sodium nitroprusside.

The presence and extent of cyanide poisoning are often initially unknown. There is no widely available, rapid, confirmatory cyanide blood test. Treatment decisions must be made on the basis of clinical history and signs and symptoms of cyanide intoxication.

Table 1. Common Signs and Symptoms of Cyanide Poisoning
Symptoms | Signs
- Headache - Confusion - Dyspnea - Chest Tightness - Nausea | - Altered Mental Status (e.g., confusion, disorientation) - Seizures or Coma - Mydriasis - Tachypnea/Hyperpnea (early) - Bradypnea/Apnea (late) - Hypertension (early)/ Hypotension (late) - Cardiovascular Collapse - Vomiting - Plasma Lactate Concentration ≥ 8 mmol/L

In some settings, panic symptoms including tachypnea and vomiting may mimic early cyanide poisoning signs. The presence of altered mental status (e.g., confusion and disorientation) and/or mydriasis is suggestive of true cyanide poisoning although these signs can occur with other toxic exposures as well.

Smoke Inhalation

Not all smoke inhalation victims will have cyanide poisoning and may present with burns, trauma, and exposure to other toxic substances making a diagnosis of cyanide poisoning particularly difficult. Prior to administration of NITHIODOTE, smoke-inhalation victims should be assessed for the following:

- Exposure to fire or smoke in an enclosed area
- Presence of soot around the mouth, nose, or oropharynx
- Altered mental status

Although hypotension is highly suggestive of cyanide poisoning, it is only present in a small percentage of cyanide-poisoned smoke inhalation victims. Also indicative of cyanide poisoning is a plasma lactate concentration greater than or equal to 10 mmol/L (a value higher than that typically listed in the table of signs and symptoms of isolated cyanide poisoning because carbon monoxide associated with smoke inhalation also contributes to lactic acidemia). If cyanide poisoning is suspected, treatment should not be delayed in order to obtain a plasma lactate concentration.

Use with Other Cyanide Antidotes

The safety of administering other cyanide antidotes simultaneously with NITHIODOTE has not been established. If a decision is made to administer another cyanide antidote with NITHIODOTE, these drugs should not be administered concurrently in the same intravenous (IV) line. [see Dosage and Administration (2.2)]

2.2 Recommended Dosing

Sodium nitrite injection and sodium thiosulfate injection are administered by slow intravenous injection. They should be given as early as possible after a diagnosis of acute serious or life-threatening cyanide poisoning has been established. Sodium nitrite should be administered first, followed immediately by sodium thiosulfate. Blood pressure must be monitored during infusion in both adults and children. The rate of infusion should be decreased if significant hypotension is noted.

Age | Intravenous Dose of Sodium Nitrite and Sodium Thiosulfate
Adults | 1) Sodium Nitrite -10 mL of sodium nitrite at the rate of 2.5 to 5 mL/minute 2) Sodium Thiosulfate - 50 mL of sodium thiosulfate immediately following administration of sodium nitrite.
Children | 1) Sodium Nitrite - 0.2 mL/kg (6 mg/kg or 6-8 mL/m^2 BSA) of sodium nitrite at the rate of 2.5 to 5 mL/minute not to exceed 10 mL 2) Sodium Thiosulfate - 1 mL/kg of body weight (250 mg/kg or approximately 30-40 mL/m^2 of BSA) not to exceed 50 mL total dose immediately following administration of sodium nitrite.

NOTE: If signs of poisoning reappear, repeat treatment using one-half the original dose of both sodium nitrite and sodium thiosulfate.

In adult and pediatric patients with known anemia, it is recommended that the dosage of sodium nitrite should be reduced proportionately to the hemoglobin concentration. [see Warnings and Precautions (5.2)]

Visually inspect all parenteral drug products for particulate matter and discoloration prior to administration.

2.3 Recommended Monitoring

Monitor patients for at least 24-48 hours after NITHIODOTE administration for adequacy of oxygenation and perfusion and for recurrent signs and symptoms of cyanide toxicity. When possible, obtain hemoglobin/hematocrit when treatment is initiated. Measurements of oxygen saturation using standard pulse oximetry and calculated oxygen saturation values based on measured PO2 are unreliable in the presence of methemoglobinemia.

Methemoglobin level: Administrations of sodium nitrite solely to achieve an arbitrary level of methemoglobinemia may be unnecessary and potentially hazardous. The therapeutic effects of sodium nitrite do not appear to be mediated by methemoglobin formation alone [see Clinical Pharmacology (12)] and clinical responses to sodium nitrite administration have been reported in association with methemoglobin levels of less than 10%. Administration of sodium nitrite beyond the initial dose should be guided primarily by clinical response to treatment (i.e., a second dose should be considered only if there is inadequate clinical response to the first dose). It is generally recommended that methemoglobin concentrations be closely monitored and kept below 30%. Monitor serum methemoglobin levels during treatment using co-oximetry, and discontinue administration of sodium nitrite when methemoglobin levels exceed 30%. Intravenous methylene blue and exchange transfusion have been reported in the literature as treatments for life-threatening methemoglobinemia.

2.4 Incompatibility Information

Chemical incompatibility has been reported between NITHIODOTE and hydroxocobalamin and these drugs should not be administered simultaneously through the same IV line. No chemical incompatibility has been reported between sodium thiosulfate and sodium nitrite, when administered sequentially through the same IV line as described in Dosage and Administration.

Simultaneous administration of NITHIODOTE and blood products (whole blood, packed red cells, platelet concentrate and/or fresh frozen plasma) through the same intravenous line is not recommended. However, blood products and NITHIODOTE can be administered simultaneously using separate intravenous lines (preferably on contralateral extremities, if peripheral lines are being used).

3 DOSAGE FORMS AND STRENGTHS

NITHIODOTE Injection consists of:

- One vial of sodium nitrite injection, USP 300 mg/10 mL (30 mg/mL) and
- One vial of sodium thiosulfate injection USP 12.5 grams/50 mL (250 mg/mL)

Administration of one vial of each medication constitutes a single dose.

4 CONTRAINDICATIONS

None

5 WARNINGS AND PRECAUTIONS

5.1 Hypotension

Sodium nitrite has been associated with severe hypotension, methemoglobinemia, and death at doses less than twice recommended therapeutic doses. Hypotension may occur concurrently or separately. Sodium nitrite should be used to treat life-threatening cyanide poisoning. When the diagnosis of cyanide poisoning is uncertain and/or the patient is not in extremis, special consideration should be given to administration of sodium nitrite if the patient is known or suspected to have diminished oxygen or cardiovascular reserve (e.g., smoke inhalation victims, pre-existing anemia, substantial blood loss, cardiac or respiratory compromise) or to be at higher risk of developing methemoglobinemia (e.g., congenital methemoglobin reductase deficiency).

5.2 Methemoglobinemia

Supportive care alone may be sufficient treatment without administration of antidotes for many cases of cyanide intoxication, particularly in conscious patients without signs of severe toxicity. Monitor patients closely to ensure adequate perfusion and oxygenation during treatment with sodium nitrite.

Monitor methemoglobin levels and administer oxygen during treatment with sodium nitrite whenever possible. When sodium nitrite is administered to humans a wide range of methemoglobin concentrations occur. Methemoglobin concentrations as high as 58% have been reported after two 300-mg doses of sodium nitrite administered to an adult. Sodium nitrite should be used with caution in the presence of other drugs that may cause methemoglobinemia such as procaine and nitroprusside. Use sodium nitrite with caution in patients who may be particularly susceptible to injury from vasodilation and its related hemodynamic sequelae. Monitor hemodynamics closely during and after administration of sodium nitrite and sodium thiosulfate, and reduce infusion rates if hypotension occurs.

5.3 Anemia

Use sodium nitrite with caution in patients with known anemia. Patients with anemia will form more methemoglobin (as a percentage of total hemoglobin) than persons with normal red blood cell (RBC) volumes. Optimally, these patients should receive a sodium nitrite dose that is reduced in proportion to their oxygen carrying capacity.

5.4 Smoke Inhalation Injury

Use sodium nitrite with caution in persons with smoke inhalation injury or carbon monoxide poisoning because of the potential for worsening hypoxia due to methemoglobin formation.

5.5 Neonates and Infants

Neonates and infants may be more susceptible than adults and older pediatric patients to severe methemoglobinemia when sodium nitrite is administered. Follow reduced dosing guidelines in pediatric patients.

5.6 G6PD Deficiency

Because patients with G6PD deficiency are at increased risk of a hemolytic crisis with sodium nitrite administration, consider alternative therapeutic approaches in these patients. Monitor patients with known or suspected G6PD deficiency for an acute drop in hematocrit. Exchange transfusion may be needed for patients with G6PD deficiency who receive sodium nitrite.

5.7 Use with Other Drugs

Use sodium nitrite with caution in the presence of concomitant antihypertensive medications, diuretics or volume depletion due to diuretics, or drugs known to increase vascular nitric oxide, such as PDE5 inhibitors.

5.8 Sulfites

Sodium thiosulfate drug product may contain trace impurities of sodium sulfite. The presence of a trace amount of sulfites in this product should not deter administration of the drug for treatment of emergency situations, even if the patient is sulfite-sensitive.

6 ADVERSE REACTIONS

There have been no controlled clinical trials conducted to systematically assess the adverse events profile of sodium nitrite or sodium thiosulfate.

The medical literature has reported the following adverse events in association with sodium nitrite or sodium thiosulfate administration. These adverse events were not reported in the context of controlled trials or with consistent monitoring and reporting methodologies for adverse events. Therefore, frequency of occurrence of these adverse events cannot be assessed.

Sodium Nitrite

Cardiovascular system: syncope, hypotension, tachycardia, methemoglobinemia, palpitations, dysrhythmia

Hematological: methemoglobinemia

Central nervous system: headache, dizziness, blurred vision, seizures, confusion, coma

Gastrointestinal system: nausea, vomiting, abdominal pain

Respiratory system: tachypnea, dyspnea

Body as a Whole: anxiety, diaphoresis, lightheadedness, injection site tingling, cyanosis, acidosis, fatigue, weakness, urticaria, generalized numbness and tingling

Severe hypotension, methemoglobinemia, cardiac dysrhythmias, coma and death have been reported in patients without life-threatening cyanide poisoning but who were treated with injection of sodium nitrite at doses less than twice those recommended for the treatment of cyanide poisoning.

Sodium Thiosulfate

Cardiovascular system: hypotension

Central nervous system: headache, disorientation

Gastrointestinal system: nausea, vomiting

Hematological: prolonged bleeding time

Body as a Whole: salty taste in mouth, warm sensation over body

In humans, rapid administration of concentrated solutions or solutions not freshly prepared, and administration of large doses of sodium thiosulfate have been associated with a higher incidence of nausea and vomiting. However, administration of 0.1 g sodium thiosulfate per pound up to a maximum of 15 g in a 10-15% solution over 10-15 minutes was associated with nausea and vomiting in 7 of 26 patients without concomitant cyanide intoxication.

In a series of 11 human subjects, a single intravenous infusion of 50 mL of 50% sodium thiosulfate was associated with increases in clotting time 1-3 days after administration. However, no significant changes were observed in other hematological parameters.

7 DRUG INTERACTIONS

Formal drug interaction studies have not been conducted with NITHIODOTE.

8 USE IN SPECIFIC POPULATIONS

8.1 Pregnancy

Risk Summary

Life-sustaining therapy should not be withheld. Cyanide poisoning is a medical emergency in pregnancy, which can be fatal for the pregnant woman and fetus if left untreated (see Clinical Considerations). Therefore, if a pregnant woman has known or suspected cyanide poisoning, Sodium Nitrite Injection for sequential use with Sodium Thiosulfate Injection is recommended [see Indications and Usage (1)]. There are no available data on NITHIODOTE use in pregnant women to establish a drug-associated risk for major birth defects, miscarriage, or adverse maternal or fetal outcomes. If available, consider alternative therapies not associated with methemoglobinemia.

There are no intravenous animal studies to evaluate the effect of sodium nitrite, sodium thiosulfate, or the combination on embryofetal development. In published animal studies, fetal mortality was reported when pregnant guinea pigs were subcutaneously administered sodium nitrite at 1.7 times the maximum recommended human dose (MRHD) of 450 mg sodium nitrite when maternal and fetal methemoglobin concentrations were at their peak. In other published studies, no evidence of malformations were reported in guinea pigs, mice, or rats; however, severe anemia, reduced growth, and increased pup mortality was reported when pregnant rats were treated with 4.7 times the MRHD of sodium nitrite via drinking water during gestation and throughout lactation.

In published animal studies, no evidence of embryotoxicity or malformations was reported when sodium thiosulfate was administered orally during organogenesis to pregnant mice, rats, hamsters, or rabbits at 0.2 to 0.9 times the human daily dose of 12.5 g for cyanide poisoning. The sodium thiosulfate studies did not test doses that were comparable to the human dose for cyanide poisoning (see Data).

Clinical Considerations

Disease-associated maternal and/or embryo/fetal risk

Cyanide readily crosses the placenta. Cyanide poisoning is a medical emergency in pregnancy, which can be fatal for the pregnant woman and fetus if left untreated. Treatment for cyanide poisoning should not be withheld because of potential concerns regarding the effects of Nithiodote on the fetus.

Fetal/neonatal adverse reactions

Sodium nitrite produces methemoglobin. Fetal hemoglobin is oxidized to methemoglobin more easily than adult hemoglobin. In addition, the fetus has lower levels of methemoglobin reductase than adults [see Use in Specific Populations (8.4)]. Based on animal studies, prenatal exposure to sodium nitrite resulted in impaired neural development likely the result of prenatal hypoxia (see Data). If available, consider alternative therapy not known to be associated with methemoglobinemia.

Data

Animal Data

Sodium nitrite

There are no intravenous toxicology studies of sodium nitrite that evaluate the potential for reproductive and developmental toxicity. In a published study, sodium nitrite treatment of pregnant guinea pigs with 60 or 70 mg/kg/day resulted in abortion of the litters within 1-4 days of treatment. All animals treated subcutaneously with 70 mg/kg, sodium nitrite died within 60 minutes of treatment. Further studies demonstrated that a dose of 60 mg/kg resulted in measurable blood levels of methemoglobin in the dams and their fetuses for up to 6 hours post treatment. Maternal methemoglobin levels were higher than the levels in the offspring at all times measured. Based on a body surface area comparison, a 60 mg/kg dose in the guinea pig that resulted in death was only 1.7 times higher than the highest clinical dose of sodium nitrite that would be used to treat cyanide poisoning (based on a body surface area comparison).

In a published study, treatment of pregnant rats via drinking water with sodium nitrite at concentrations of either 2000 or 3000 mg/L during gestation and throughout lactation resulted in severe anemia, reduced growth, and increased mortality in the offspring. This exposure regimen in the rat model would result in dosing of approximately 220 and 300 mg/kg/day (4.7 and 6.5 times the highest clinical dose of sodium nitrite that would be used to treat cyanide poisoning, based on a body surface area comparison).

In a published study, treatment of pregnant mice with approximately 243 mg/kg sodium nitrite daily (2.6 times the maximum recommended daily dose of 450 mg/day based on body surface are) via the drinking water (1000 mg/L) from Gestation Day 7-18 did not result in evidence of malformations or embryofetal toxicity or maternal toxicity.

Behavioral and neurodevelopmental studies in rats suggest persistent effects of prenatal exposure to sodium nitrite that were detectable postnatally. Specifically, animals that were exposed prenatally to sodium nitrite (2000 mg/L via drinking water) demonstrated impaired discrimination learning behavior (both auditory and visual) and reduced long-term retention of the passive-avoidance response compared to control animals. Additional studies demonstrated a delay in the development of AchE and 5-HT positive fiber ingrowth into the hippocampal dentate gyrus and parietal neocortex during the first week of life of prenatal nitrite treated pups. These changes have been attributed to prenatal hypoxia following nitrite exposure.

Sodium thiosulfate

No malformations or evidence of embryo-fetal toxicity were noted when pregnant mice, rats, hamsters, or rabbits were administered oral doses of sodium thiosulfate of up to 550, 400, 400, or 580 mg/kg, respectively during organogenesis (0.2, 0.3, 0.26, and 0.9 times the human dose of 12.5 g/60 kg person for cyanide poisoning based on body surface area). Published studies suggest that treatment with sodium thiosulfate ameliorates the teratogenic effects of maternal cyanide poisoning in hamsters.

8.2 Lactation

Risk Summary

There are no data on the presence of sodium nitrite or sodium thiosulfate in human or animal milk, the effects on the breastfed infant, or the effects on milk production. Cyanide and thiocyanate (which is formed when sodium thiosulfate combines with cyanide) are present in human milk. Because of the potential for serious adverse reactions in the breastfed infant, breastfeeding is not recommended during treatment with NITHIODOTE. There are no data to determine when breastfeeding may be safely restarted following the administration of NITHIODOTE.

8.4 Pediatric Use

There are case reports in the medical literature of sodium nitrite in conjunction with sodium thiosulfate being administered to pediatric patients with cyanide poisoning; however, there have been no clinical studies to evaluate the safety or efficacy of sodium thiosulfate or sodium nitrite in the pediatric population. As for adult patients, dosing recommendations for pediatric patients have been based on theoretical calculations of antidote detoxifying potential, extrapolation from animal experiments, and a small number of human case reports.

Use Sodium nitrite with caution in patients less than 6 months of age because they may be at higher risk of developing severe methemoglobinemia compared to older children and adults. The presence of fetal hemoglobin, which is oxidized to methemoglobin more easily than adult hemoglobin, and lower methemoglobin reductase levels compared to older children and adults may contribute to risk.

Mortality attributed to sodium nitrite was reported following administration of an adult dose (300 mg IV followed by a second dose of 150 mg) to a 17-month old child. [see Dosage and Administration (2), Warnings and Precautions, (5), Adverse Reactions (6)]

8.5 Geriatric Use

Sodium nitrite and sodium thiosulfate are known to be substantially excreted by the kidney, and the risk of adverse reactions to these drugs may be greater in patients with impaired renal function. Because elderly patients are more likely to have decreased renal function, care should be taken in dose selection, and it may be useful to monitor renal function.

8.6 Renal Impairment

Sodium nitrite and sodium thiosulfate are known to be substantially excreted by the kidney, and the risk of toxic reactions to these drugs may be greater in patients with impaired renal function. Because elderly patients are more likely to have decreased renal function, care should be taken in dose selection, and it may be useful to monitor renal function.

10 OVERDOSAGE

Sodium Nitrite

Large doses of sodium nitrite result in severe hypotension and toxic levels of methemoglobin which may lead to cardiovascular collapse.

Sodium nitrite administration has been reported to cause or significantly contribute to mortality in adults at oral doses as low as 1 g and intravenous doses as low as 600 mg. A death attributed to sodium nitrite has been reported following administration of an adult dose (300 mg IV followed by a second dose of 150 mg) to a 17-month old child.

Cyanosis may become apparent at a methemoglobin level of 10-20%. Other clinical signs and symptoms of sodium nitrite toxicity (anxiety, dyspnea, nausea, and tachycardia) can be apparent at methemoglobin levels as low as 15%. More serious signs and symptoms, including cardiac dysrhythmias, circulatory failure, and central nervous system depression are seen as methemoglobin levels increase, and levels above 70% are usually fatal.

Treatment of overdose involves supplemental oxygen and supportive measures such as exchange transfusion. Treatment of severe methemoglobinemia with intravenous methylene blue has been described in the medical literature; however, this may also cause release of cyanide bound to methemoglobin. Because hypotension appears to be mediated primarily by an increase in venous capacitance, measures to increase venous return may be most appropriate to treat hypotension.

Sodium Thiosulfate

There is limited information about the effects of large doses of sodium thiosulfate in humans. Oral administration of 3 g sodium thiosulfate per day for 1-2 weeks in humans resulted in reductions in room air arterial oxygen saturation to as low as 75%, which was due to a rightward shift in the oxygen hemoglobin dissociation curve. The subjects returned to baseline oxygen saturations 1 week after discontinuation of sodium thiosulfate. A single intravenous administration of 20 mL of 10% sodium thiosulfate reportedly did not change oxygen saturations.

11 DESCRIPTION

Sodium nitrite, one of the active ingredients in NITHIODOTE has the chemical name nitrous acid sodium salt. The chemical formula is NaNO2 and the molecular weight is 69.0. Sodium thiosulfate, the second active ingredient in NITHIODOTE has the chemical name thiosulfuric acid, disodium salt, pentahydrate. The chemical formula is Na2S2O3∙ 5H2O and the molecular weight is 248.17. The structural formulae are:

Structure of Sodium Nitrite

Structure of Sodium Thiosulfate Pentahydrate

NITHIODOTE is a cyanide antidote which contains one 10 mL glass vial of a 3% solution of sodium nitrite injection and one 50 mL glass vial containing a 25% solution of sodium thiosulfate injection.

Sodium nitrite injection is a sterile aqueous solution and is intended for intravenous injection. Each vial contains 300 mg of sodium nitrite in 10 mL solution (30 mg/mL). Sodium nitrite injection is a clear solution with a pH between 7.0 and 9.0.

Sodium thiosulfate injection is a sterile aqueous solution and is intended for intravenous injection. Each vial contains 12.5 grams of sodium thiosulfate in 50 mL solution (250 mg/mL). Each mL also contains 2.8 mg boric acid and 4.4 mg of potassium chloride. The pH of the solution is adjusted with boric acid and/or sodium hydroxide. Sodium thiosulfate injection is a clear solution with a pH between 7.5 and 9.0.

12 CLINICAL PHARMACOLOGY

12.1 Mechanism of Action

Cyanide is an extremely toxic poison. In the absence of rapid and adequate treatment, exposure to a high dose of cyanide can result in death within minutes due to the inhibition of cytochrome oxidase resulting in arrest of cellular respiration. Specifically, cyanide binds rapidly with cytochrome a3, a component of the cytochrome c oxidase complex in mitochondria. Inhibition of cytochrome a3 prevents the cell from using oxygen and forces anaerobic metabolism, resulting in lactate production, cellular hypoxia and metabolic acidosis. In massive acute cyanide poisoning, the mechanism of toxicity may involve other enzyme systems as well. Signs and symptoms of acute systemic cyanide poisoning may develop rapidly within minutes, depending on the route and extent of cyanide exposure.

The synergy resulting from treatment of cyanide poisoning with the combination of sodium nitrite and sodium thiosulfate is the result of differences in their primary mechanisms of action as antidotes for cyanide poisoning.

Sodium Nitrite

Sodium nitrite is thought to exert its therapeutic effect by reacting with hemoglobin to form methemoglobin, an oxidized form of hemoglobin incapable of oxygen transport but with high affinity for cyanide. Cyanide preferentially binds to methemoglobin over cytochrome a3, forming the nontoxic cyanomethemoglobin. Methemoglobin displaces cyanide from cytochrome oxidase, allowing resumption of aerobic metabolism. The chemical reaction is as follows:

NaNO2 + Hemoglobin → Methemoglobin
HCN + Methemoglobin → Cyanomethemoglobin

Vasodilation has also been cited to account for at least part of the therapeutic effect of sodium nitrite. It has been suggested that sodium nitrite-induced methemoglobinemia may be more efficacious against cyanide poisoning than comparable levels of methemoglobinemia induced by other oxidants. Also, sodium nitrite appears to retain some efficacy even when the formation of methemoglobin is inhibited by methylene blue.

Sodium Thiosulfate

The primary route of endogenous cyanide detoxification is by enzymatic transulfuration to thiocyanate (SCN^-), which is relatively nontoxic and readily excreted in the urine. Sodium thiosulfate is thought to serve as a sulfur donor in the reaction catalyzed by the enzyme rhodanese, thus enhancing the endogenous detoxification of cyanide in the following chemical reaction:

Rhodanese

Na2S2O3 + CN^- → SCN^- + Na2SO3.

12. 2 Pharmacodynamics

Sodium Nitrite

When 4 mg/kg sodium nitrite was administered intravenously to six healthy human volunteers, the mean peak methemoglobin concentration was 7%, achieved at 30-60 minutes after injection, consistent with reports in cyanide poisoning victims. Supine systolic and diastolic blood pressures dropped approximately 20% within 10 minutes, a drop which was sustained throughout the 40 minutes of testing. This was associated with a 20 beat per minute increase in pulse rate that returned to baseline in 10 minutes. Five of these subjects were unable to withstand orthostatic testing due to fainting. One additional subject, who received a 12 mg/kg dose of sodium nitrite, experienced severe cardiovascular effects and achieved a peak methemoglobin concentration of 30% at 60 minutes following injection.

Oral doses of 120 to 180 mg of sodium nitrite administered to healthy volunteers caused minimal cardiovascular changes when subjects were maintained in the horizontal position. However, minutes after being placed in the upright position subjects exhibited tachycardia and hypotension with syncope.

The half life for conversion of methemoglobin to normal hemoglobin in a cyanide poisoning victim who has been administered sodium nitrite and sodium thiosulfate is estimated to be 55 minutes.

Sodium Thiosulfate

In dogs, pretreatment with sodium thiosulfate to achieve a steady state level of 2 μmol/mL increased the rate of conversion of cyanide to thiocyanate over 30-fold.

12.3 Pharmacokinetics

Sodium Nitrite

Sodium nitrite is a strong oxidant and reacts rapidly with hemoglobin to form methemoglobin. The pharmacokinetics of free sodium nitrite in humans have not been well studied. It has been reported that approximately 40% of sodium nitrite is excreted unchanged in the urine while the remaining 60% is metabolized to ammonia and related small molecules.

Sodium Thiosulfate

Thiosulfate taken orally is not systemically absorbed. Most of the thiosulfate is oxidized to sulfate or is incorporated into endogenous sulphur compounds; a small proportion is excreted through the kidneys. Approximately 20-50% of exogenously administered thiosulfate is eliminated unchanged via the kidneys. After an intravenous injection of 1 g sodium thiosulfate in patients, the reported serum thiosulfate half-life was approximately 20 minutes. However, after an intravenous injection of a substantially higher dose of sodium thiosulfate (150 mg/kg, that is, 9 g for 60 kg body weight) in normal healthy men, the reported elimination half-life was 182 minutes.

Cyanide

The apparent terminal elimination half life and volume of distribution of cyanide, in a patient treated for an acute cyanide poisoning with sodium nitrite and sodium thiosulfate administration, have been reported to be 19 hours and 0.41 L/kg, respectively. Additionally, an initial elimination half life of cyanide has been reported to be approximately 1-3 hours.

Thiocyanate

After detoxification, in healthy subjects, thiocyanate is excreted mainly in the urine at a rate inversely proportional to creatinine clearance. In healthy subjects, the elimination half-life and volume of distribution of thiocyanate have been reported to be 2.7 days and 0.25 L/kg, respectively. However, in subjects with renal insufficiency the reported elimination half life is approximately 9 days.

13 NONCLINICAL TOXICOLOGY

13.1 Carcinogenesis, Mutagenesis, Impairment of Fertility

Carcinogenesis:

Sodium Nitrite

The potential benefit of an acute exposure to sodium nitrite as part of a cyanide antidote outweighs concerns raised by the equivocal findings in chronic rodent studies. Sodium nitrite (0, 750, 1500, or 3000 ppm equivalent to average daily doses of approximately 0, 35, 70, or 130 mg/kg for males and 0, 40, 80, or 150 mg/kg for females) was orally administered to rats (Fischer 344 strain) for 2 years via drinking water. There were no significant increases in the incidence of tumor in either male or female rats. Sodium nitrite (0, 750, 1500, or 3000 ppm equivalent to average daily doses of approximately 0, 60, 120, or 220 mg/kg for males and 0, 45, 90, or 165 mg/kg for females) was administered to B6C3F1 mice for 2 years via the drinking water. Equivocal results were obtained in female mice. Specifically, there was a positive trend toward an increase in the incidence of squamous cell papilloma or carcinoma in the forestomach of female mice. Although the incidence of hyperplasia of the glandular stomach epithelium was significantly greater in the high-dose male mice compared to controls, there were no significant increases in tumors in the male mice. Numerous reports in the published literature indicate that sodium nitrite may react in vivo with secondary amines to form carcinogenic nitrosamines in the stomach. Concurrent exposure to sodium nitrite and secondary amines in feed or drinking water resulted in an increase in the incidence of tumors in rodents.

Sodium Thiosulfate

Long-term studies in animals have not been performed to evaluate the potential carcinogenicity of sodium thiosulfate.

Mutagenesis:

Sodium Nitrite

Sodium nitrite is mutagenic in S. typhimurium strains TA100, TA1530, TA1535 with and without metabolic activation; however, it was negative in strain TA98, TA102, DJ460 and E. coli strain WP2UVRA/PKM101. Sodium nitrite has been reported to be genotoxic to V79 hamster cells in vitro and in the mouse lymphoma assay, both assays conducted in the absence of metabolic activation. Sodium nitrite was negative in the in vitro chromosomal aberrations assay using human peripheral blood lymphocytes. Acute administration of sodium nitrite to male rats or male mice did not produce an increased incidence of micronuclei in bone marrow. Likewise, sodium nitrite administration to mice for 14-weeks did not result in an increase in the incidence of micronuclei in the peripheral blood.

Sodium Thiosulfate

The mutagenic potential of sodium thiosulfate has been examined in the in vitro Bacterial Reverse Mutation Assay (Ames Assay). Sodium thiosulfate was not mutagenic in the absence of metabolic activation in S. typhimurium strains TA98, TA100, TA1535, TA537, or TA1538. Sodium thiosulfate was not mutagenic in the presence of metabolic activation in strains TA 98, TA1535, TA1537, TA1538 or E. coli strain WP2.

Impairment of Fertility:

Sodium Nitrite

Multigenerational fertility and reproduction studies conducted by the National Toxicology Program did not detect any evidence of an effect of sodium nitrite (0.0, 0.06, 0.12, and 0.24% weight/volume) on either fertility or any reproductive parameter in Swiss CD-1 mice. This treatment protocol resulted in approximate doses of 125, 260, and 425 mg/kg/day. The highest exposure in this mouse study is 4.6 times greater than the highest clinical dose of sodium nitrite that would be used to treat cyanide poisoning (based on a body surface area comparison).

Sodium Thiosulfate

There are no preclinical studies examining the effects of sodium thiosulfate on fertility.

14 CLINICAL STUDIES

Human Data

The human data supporting the use of sodium thiosulfate for cyanide poisoning consists primarily of published case reports. There are no randomized controlled clinical trials. Nearly all the human data describing the use of sodium thiosulfate report its use in conjunction with sodium nitrite. Dosing recommendations for humans have been based on theoretical calculations of antidote detoxifying potential, extrapolation from animal experiments, and a small number of human case reports.

There have been no human studies to prospectively and systematically evaluate the safety of sodium thiosulfate or sodium nitrite in humans. Available human safety information is based largely on anecdotal case reports and case series of limited scope.

Animal Data (Cyanide Poisoning)

THE EFFECTIVENESS OF SODIUM THIOSULFATE AND SODIUM NITRITE FOR THE TREATMENT OF ACUTE CYANIDE POISONING HAS NOT BEEN STUDIED IN HUMANS IN ADEQUATE AND WELL-CONTROLLED CLINICAL TRIALS BECAUSE INDUCING THE CONDITION IN HUMANS TO STUDY THE DRUG'S EFFICACY IS NOT ETHICAL.

Due to the extreme toxicity of cyanide, experimental evaluation of treatment efficacy has predominantly been completed in animal models. The efficacy of sodium thiosulfate treatment alone to counteract the toxicity of cyanide was initially reported in 1895 by Lang. The efficacy of amyl nitrite treatment in cyanide poisoning of the dog model was first reported in 1888 by Pedigo. Further studies in the dog model, which demonstrated the utility of sodium nitrite as a therapeutic intervention, were reported in 1929 by Mladoveanu and Gheorghiu. However, Hugs and Chen et al. independently reported upon the superior efficacy of the combination of sodium nitrite and sodium thiosulfate in 1932-1933. Treatment consisted of intravenously administered 22.5 mg/kg (half the lethal dose) sodium nitrite or 1 g/kg sodium thiosulfate alone or in sequence immediately after subcutaneous injection of sodium cyanide into dogs over a range of doses. Subsequent doses of 10 mg/kg sodium nitrite and/or 0.5 g/kg sodium thiosulfate were administered when clinical signs or symptoms of poisoning persisted or reappeared. Either therapy administered alone increased the dose of sodium cyanide required to cause death, and when administered together, sodium nitrite and sodium thiosulfate resulted in a synergistic effect in raising the lethal dose of sodium cyanide. The combined therapy appeared to have reduced efficacy when therapy was delayed until signs of poisoning (e.g. convulsions) appeared; however, other investigators have reported survival in dogs that were administered antidotal treatment after respiratory arrest had occurred.

Animal studies conducted in other species (e.g., rat, guinea pig, sheep, pigeon, and cat) have also supported a synergistic effect of intravenous sodium nitrite and sodium thiosulfate in the treatment of cyanide poisoning.

While intravenous injection of sodium nitrite and sodium thiosulfate was effective in reversing the effects of lethal doses of cyanide in dogs, intramuscular injection of sodium nitrite, with or without sodium thiosulfate, was found not to be effective in the same setting.

16 HOW SUPPLIED/STORAGE AND HANDLING

Each NITHIODOTE carton (NDC 60267-812-00) consists of the following:

- One 10 mL glass vial of sodium nitrite injection 30 mg/mL (containing 300 mg of sodium nitrite);
- One 50 mL glass vial of sodium thiosulfate injection 250 mg/mL (containing 12.5 grams of sodium thiosulfate);
- One package insert.

Storage

Store at controlled room temperature between 20°C and 25°C (68°F - 77°F); excursions permitted to 15-30°C (59 to 86°F).

Protect from direct light. Do not freeze.

17 PATIENT COUNSELING INFORMATION

NITHIODOTE is indicated for cyanide poisoning and in this setting, patients will likely be unresponsive or may have difficulty in comprehending counseling information.

Hypotension and Methemoglobin Formation

When feasible, patients should be informed of the possibility of life-threatening hypotension and methemoglobin formation.

Monitoring

Where feasible, patients should be informed of the need for close monitoring of blood pressure and oxygenation.

Lactation

Advise women that breastfeeding is not recommended during treatment with NITHIODOTE [see Use in Specific Populations (8.2)].

Hope Pharmaceuticals, Scottsdale, Arizona 85260

US PATENTS 8496973, 8568793, 9345724, and 9585912

PRINCIPAL DISPLAY PANEL - Kit Carton

NDC 60267-812-00
Rx Only

NITHIODOTE™
Sodium Nitrite Injection, USP
and
Sodium Thiosulfate Injection, USP

FOR INTRAVENOUS USE

SINGLE USE ONLY

Any unused portion of a vial should be discarded.

Box Contains:

Sodium Nitrite Injection, USP
300 mg/10 mL
(30 mg/mL)
and
Sodium Thiosulfate Injection, USP
12.5 grams/50 mL
(250 mg/mL)

Manufactured for:
HOPE
PHARMACUETICALS ™
Scottsdale, AZ 85260 U.S.A.